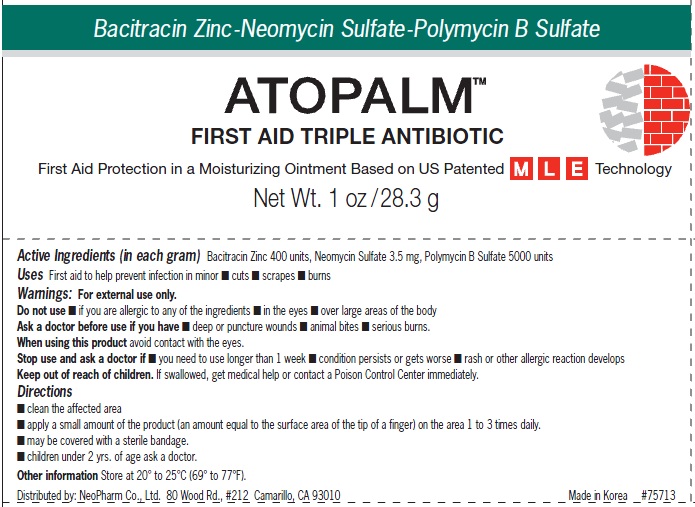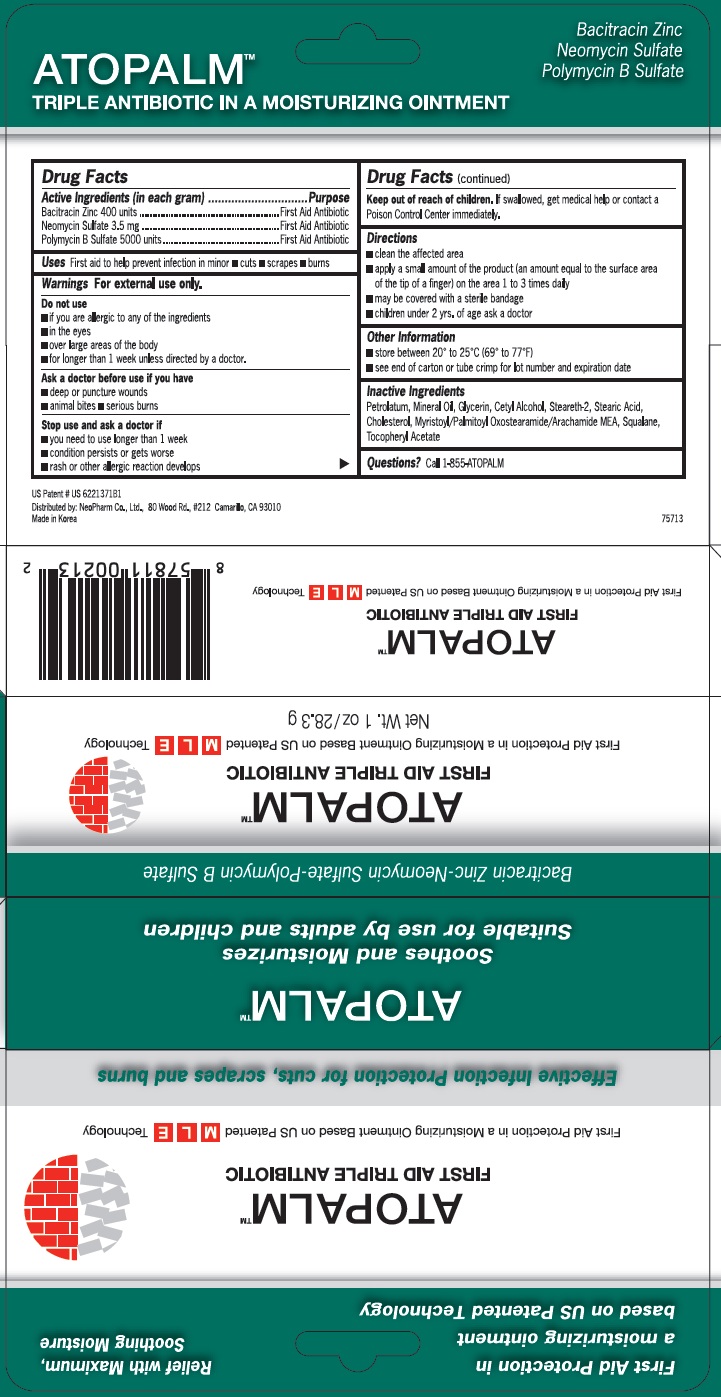 DRUG LABEL: Atopalm First Aid Triple Antibiotic
                        
NDC: 51141-3000 | Form: OINTMENT
Manufacturer: Neopharm Co., Ltd.
Category: otc | Type: HUMAN OTC DRUG LABEL
Date: 20111109

ACTIVE INGREDIENTS: BACITRACIN ZINC 400 [iU]/1 g; NEOMYCIN SULFATE 3.5 mg/1 g; POLYMYXIN B SULFATE 5000 [iU]/1 g
INACTIVE INGREDIENTS: PETROLATUM; MINERAL OIL; GLYCERIN; CETYL ALCOHOL; STEARETH-2; STEARIC ACID; CHOLESTEROL; MYRISTOYL/PALMITOYL OXOSTEARAMIDE/ARACHAMIDE MEA; SQUALENE; ACETATE ION

Atopalm First Aid Triple Antibiotic

Active Ingredients (in each gram)

Bacitracin Zinc 400 units

Neomycin Sulfate 3.5mg

Polymycin B Sulfate 5000 units

Purpose

First Aid Antibiotic

Uses

First aid to help prevent infection in minor cuts, scrapes, burns

Warnings

For external use only

Do not use

if you are allergic to any of the ingredients

in the eyes

over large areas of the body

for longer than 1 week unless director by a doctor

Ask a doctor before use if you have

deep or puncture wounds

animal bites

serious burns

Stop use and ask a doctor if

you need to use longer than 1 week

condition persists or gets worse

rash or other allergic reaction develops

Keep out of reach of children.

If swallowed, get medical help or contact a Poison Control Center immediately

Directions

clean the affected area

apply a small amount of the product (an amount equal to the surface area of the tip of a finger) on the area 1 to 3 times daily

may be covered with a sterile bandage

children under 2 yrs. of age ask a doctor

Other Information

store between 20 to 25 C (69 to 77F

see end of carton or tube crimp for lot number and expiration date.

Inactive Ingredients

Petrolatum, Mineral Oil, Glycerin, Cetyl Alcohol, Steareth-2, Stearic Acid, Cholesterol, Myristoyl/Palmitoyl Oxostearamide/Archamide MEA, Squalene, Tocopheryl Acetate

Questions?

Call 1-855-ATOPALM

PACKAGE LABEL

First Aid Protection in a moisturizing ointment based on US Patented Technology

Relief with Maximum, Soothing Moisture

ATOPALM
FIRST AID TRIPLE ANTIBIOTIC

First Aid protection in a Moisturizing Ointment Based on US Patented MLE Technology

Effective Infection Protection for cuts, scrapes and burns

ATOPALM
Soothes and Moisturizes
Suitable for use by adults and children

Bacitracin Zinc - Neomycin Sulfate - Polymycin B Sulfate

Net wt. 1oz/28.3g

Distributed by: NeoPharm Co., Ltd 80 Wood Rd, 212 Camarillo, CA 93010

Made in Korea